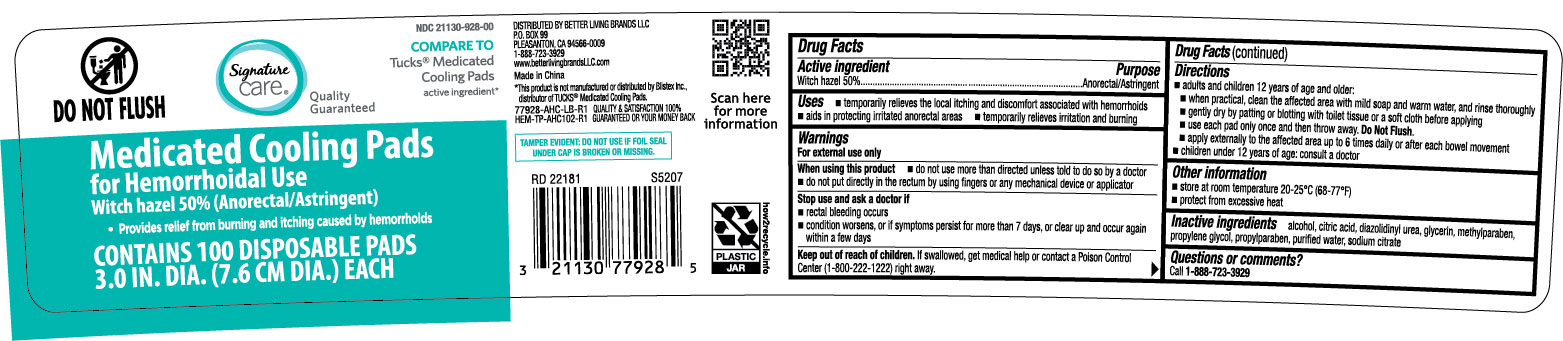 DRUG LABEL: Signature Care Medicated Cooling
NDC: 21130-928 | Form: CLOTH
Manufacturer: Better Living Brands, LLC
Category: otc | Type: HUMAN OTC DRUG LABEL
Date: 20251022

ACTIVE INGREDIENTS: WITCH HAZEL 500 mg/1 1
INACTIVE INGREDIENTS: ALCOHOL; CITRIC ACID MONOHYDRATE; METHYLPARABEN; PROPYLENE GLYCOL; PROPYLPARABEN; SODIUM CITRATE; WATER

Signature Care Medicated Cooling Pads 100ct 77928 AHC

Active ingredient Purpose

Witch hazel 50%.........................................Astringent

Uses

- temporarily relieves the local itching and discomfort associated with hemorrhoids
- aids in protecting irritated anorectal areas
- temporarily relieves irritation and burning

Warnings For external use only.

When using this product

- do not use more than directed unless told to do so by a doctor
- do not put directl in rectum by using fingersd or any mechanical device or applicator

Stop use and ask a doctor if

- rectal bleeding occurs
- condition worsens or does not improve within 7 days

Keep out of reach of children. If swallowed, get mnedical help or contact a Poison Control Center right away.

Directions

Adults:

- when practical clean the affected area with mild soap and warm water, and rinse thoroughly
- gently dry by patting or blotting with toilet tissue or a soft cloth before applying
- apply externally to the affected area up to 6 times daily or after each bowel movement
- after application, discard pad

Children under 12 years of age: ask a doctor

Other information store at 68° to 77°C (20° to 25°F)

INACTIVE INGREDIENT

Inactive ingredients alcohol, citric acid, diazol glycerin, methylparaben, propylene glycol, propylparaben, sodium citrate, water

DOSAGE AND ADMINISTRATION

DISTRIBUTED BY BETTER LIVING BRANDS LLC

P.O. BOX 99

PLEASANTON, CA 94566-0009

1-888-723-3929

www.betterlivingbrandsLLC.com

MADE IN CHINA

QUALITY & SATISFACTION 100% GUARANTEED

OR YOUR MONEY BACK